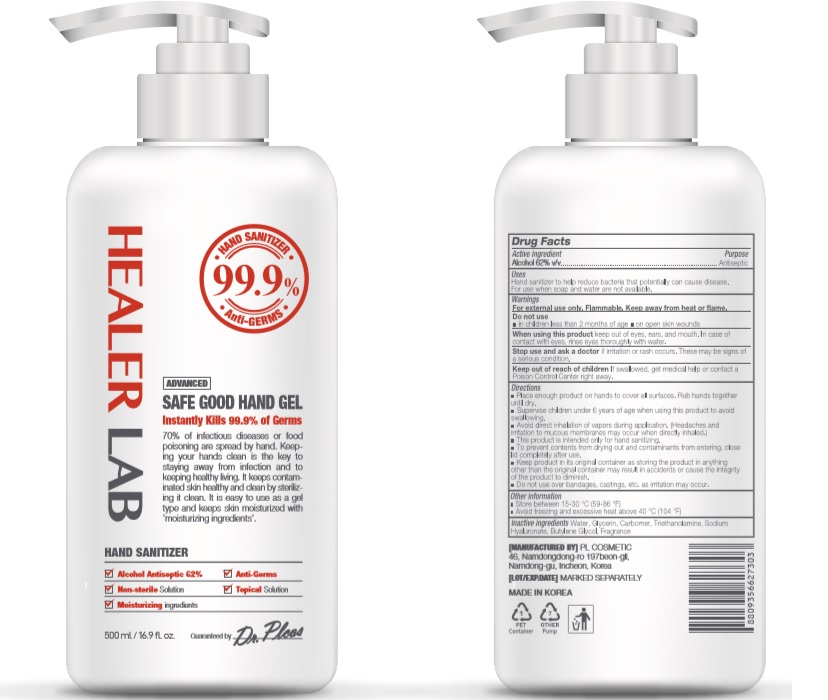 DRUG LABEL: HEALER LAB SAFE GOOD HAND Gel
NDC: 74339-0562 | Form: GEL
Manufacturer: PL COSMETIC
Category: otc | Type: HUMAN OTC DRUG LABEL
Date: 20200402

ACTIVE INGREDIENTS: ALCOHOL 310 mL/500 mL
INACTIVE INGREDIENTS: GLYCERIN; CARBOMER HOMOPOLYMER, UNSPECIFIED TYPE; WATER; BUTYLENE GLYCOL; HYALURONATE SODIUM; TROLAMINE

[HEALER LAB SAFE GOOD HAND Gel] 500 ml : 74339-0562